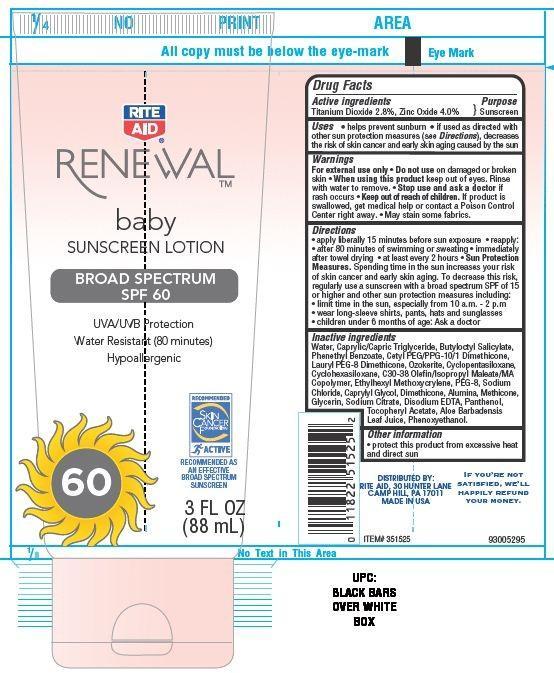 DRUG LABEL: Rite Aid RENEWAL
NDC: 11822-9027 | Form: LOTION
Manufacturer: RITE AID CORPORATION
Category: otc | Type: HUMAN OTC DRUG LABEL
Date: 20130806

ACTIVE INGREDIENTS: TITANIUM DIOXIDE 2.8 g/100 g; ZINC OXIDE 4 g/100 g
INACTIVE INGREDIENTS: WATER; TRICAPRIN; BUTYLOCTYL SALICYLATE; PHENETHYL BENZOATE; CYCLOMETHICONE 5; CYCLOMETHICONE 6; ETHYLHEXYL METHOXYCRYLENE; DIMETHICONE; .ALPHA.-TOCOPHEROL ACETATE; EDETATE DISODIUM; PANTHENOL; ALOE VERA LEAF; SODIUM CHLORIDE; ALUMINUM OXIDE; PHENOXYETHANOL; GLYCERIN; SODIUM CITRATE

Drug Facts

Active ingredients

Titanium Dioxide 2.8%

Zinc Oxide 4.0%

Purpose

Sunscreen

Warnings

For external use only.
Do not use on damaged skin or broken skin. Rinse with water to remove

When using this product keep out of eyes.

stop use and ask a doctor if rash occurs

Keep out of reach of children.

If product is swallowed, get medical help or contact a Poison Control Center right away.

May stain some fabrics.

DIRECTIONS:

- apply liberally 15 minutes before sun exposure
- reapply: after 80 minutes of swimming or sweating
- immediately after towel drying
- at least every 2 hours

Sun protection measures.

Spending time in the sun increase your risk of skin cancer and early skin aging. To decrease this risk regularly use a sunscreen with a broad spectrum SPF of 15 or higher and other sun protection measures including:

- Limit time in the sun, especially from 10 am - 2 pm
- Wear long sleeves shirts, pants, hats and sunglasses
- children under 6 month of age: Ask a doctor

OTHER INFORMATION:

protect this product from excessive heat and direct sun

Uses

- helps prevent sunburn
- if used as directed with other sun protection measures (see Directions).
- decrease the risk of skin cancer and early skin caused by the sun.

Principal Display Panel

RITE

AID

RENEWAL

baby

SUNSCREEN LOTION

BROAD SPECTRUM

SPF 60

UVA/UVB Protection

Water Resistant (80 minutes)

Hypoallergeic

RECOMMENDED

SKIN

CANCER

FOUNDATION

ACTIVE

RECOMMENDED AS

AN EFFECTIVE

BROAD SPECTRUM

SUNSCREEN

3 FL OZ

(88 mL)

INACTIVE INGREDIENTS:

Water, Caprylic Capric Triglyceride, Butyloctyl Salicylate, Phenethyl Benxoate, Cetyl PEG/PPG-10/1 Dimethicone, Laurly PEG-8 Dimethicone, Ozokerite, Cyclopentasiloxane, Cyclohexasiloxane , C30-38 Olefin/Isopropyl Maleate MA Copolymer, Ethylhexyl Methocrylene, PEG-8, Sodium Chloride, Caprylyl Glycol, Dimethicone, Alumina, Methicone, Glycerin, Sodium Citrate, Disodium EDTA, Panthenol, Tocopheryl Acetate, Aloe Barbadensis Leaf Juice, Phenoxyethanol.